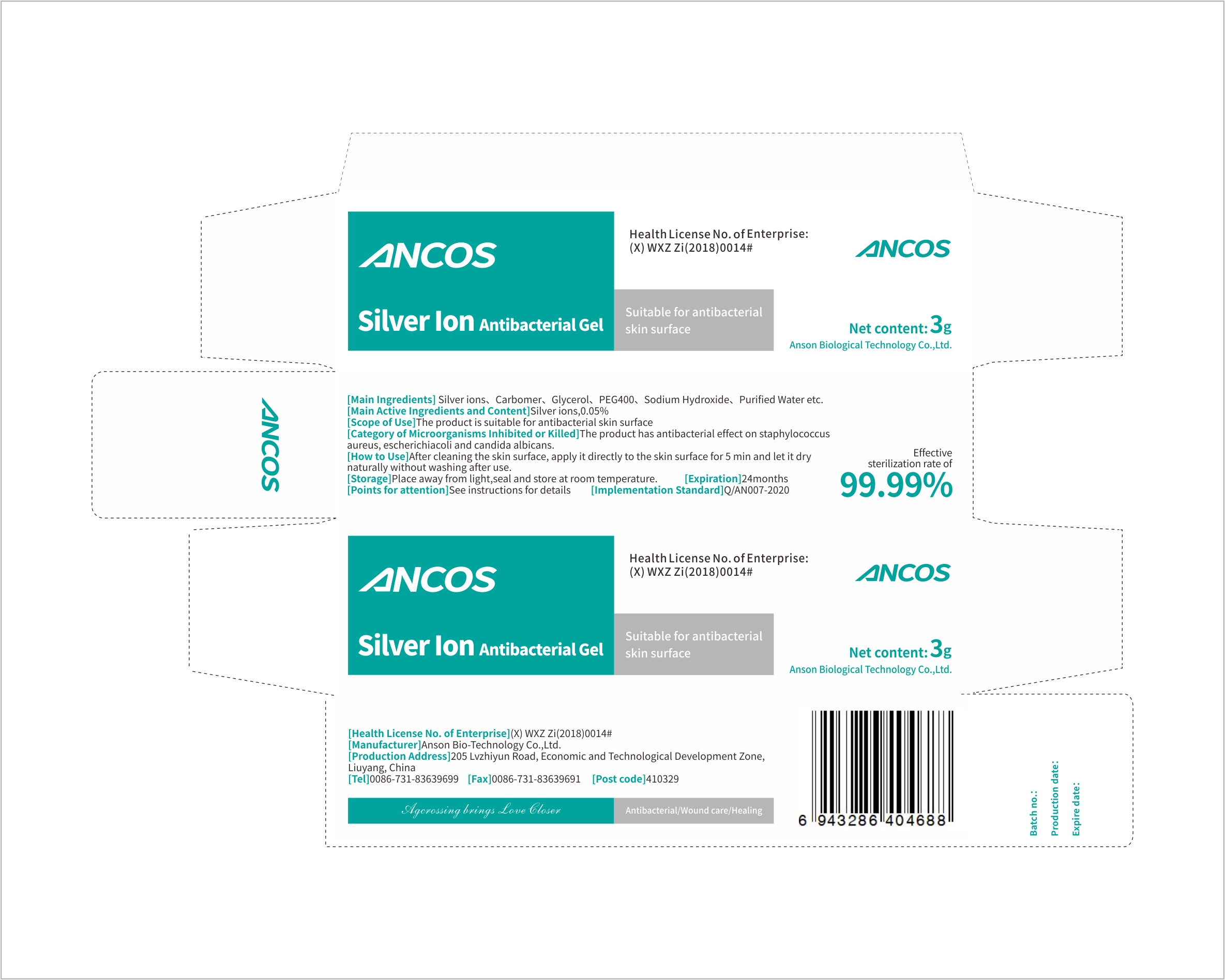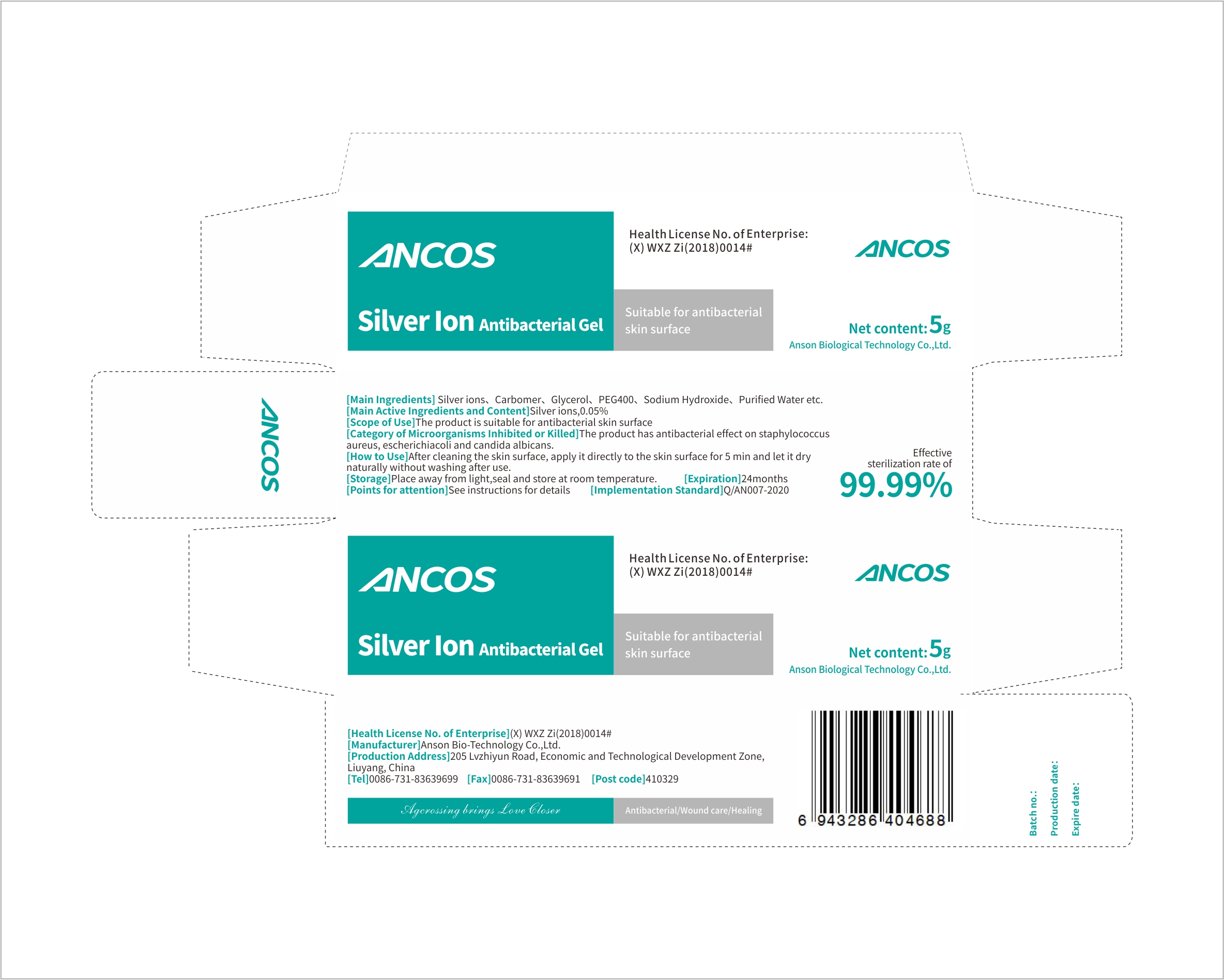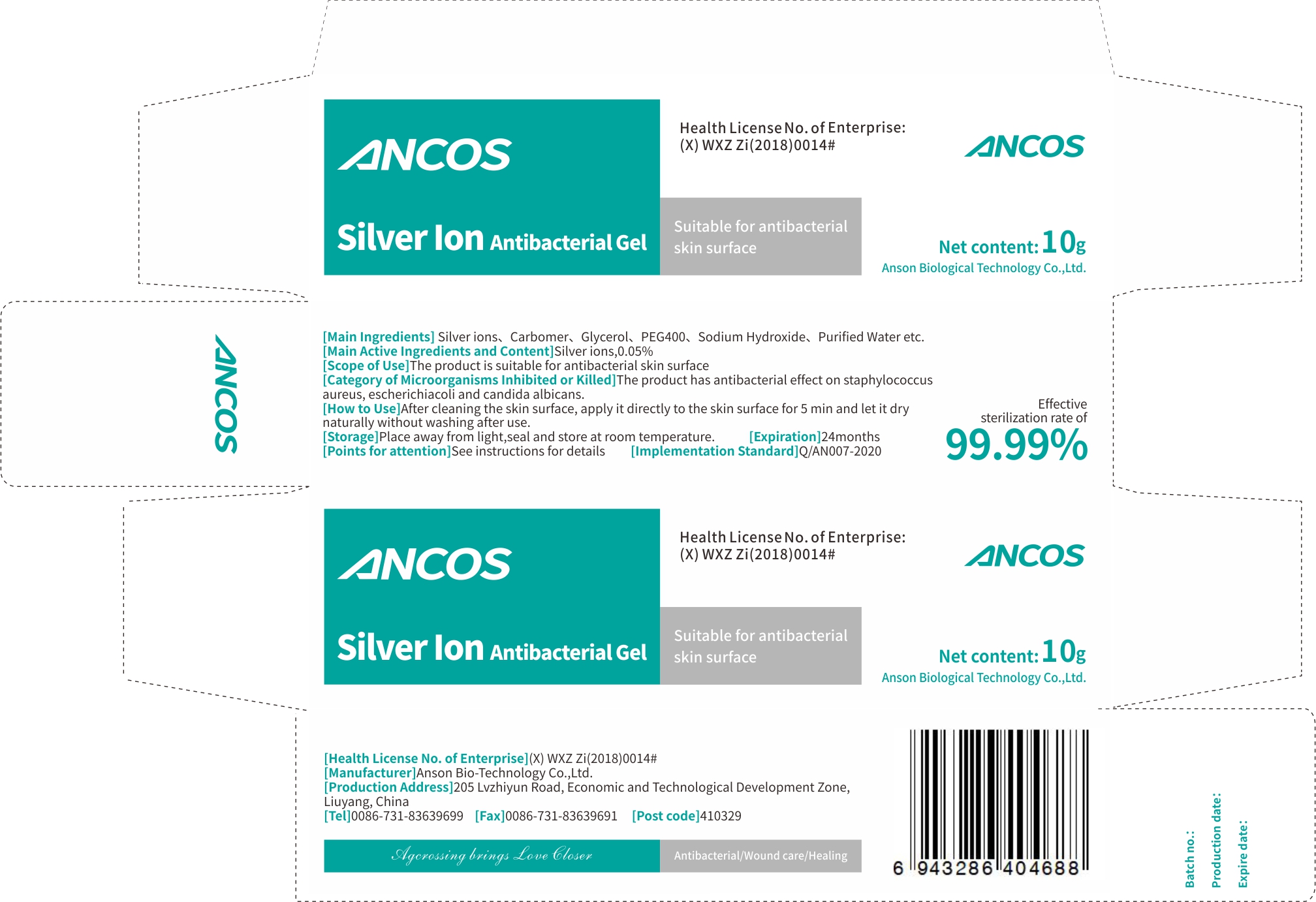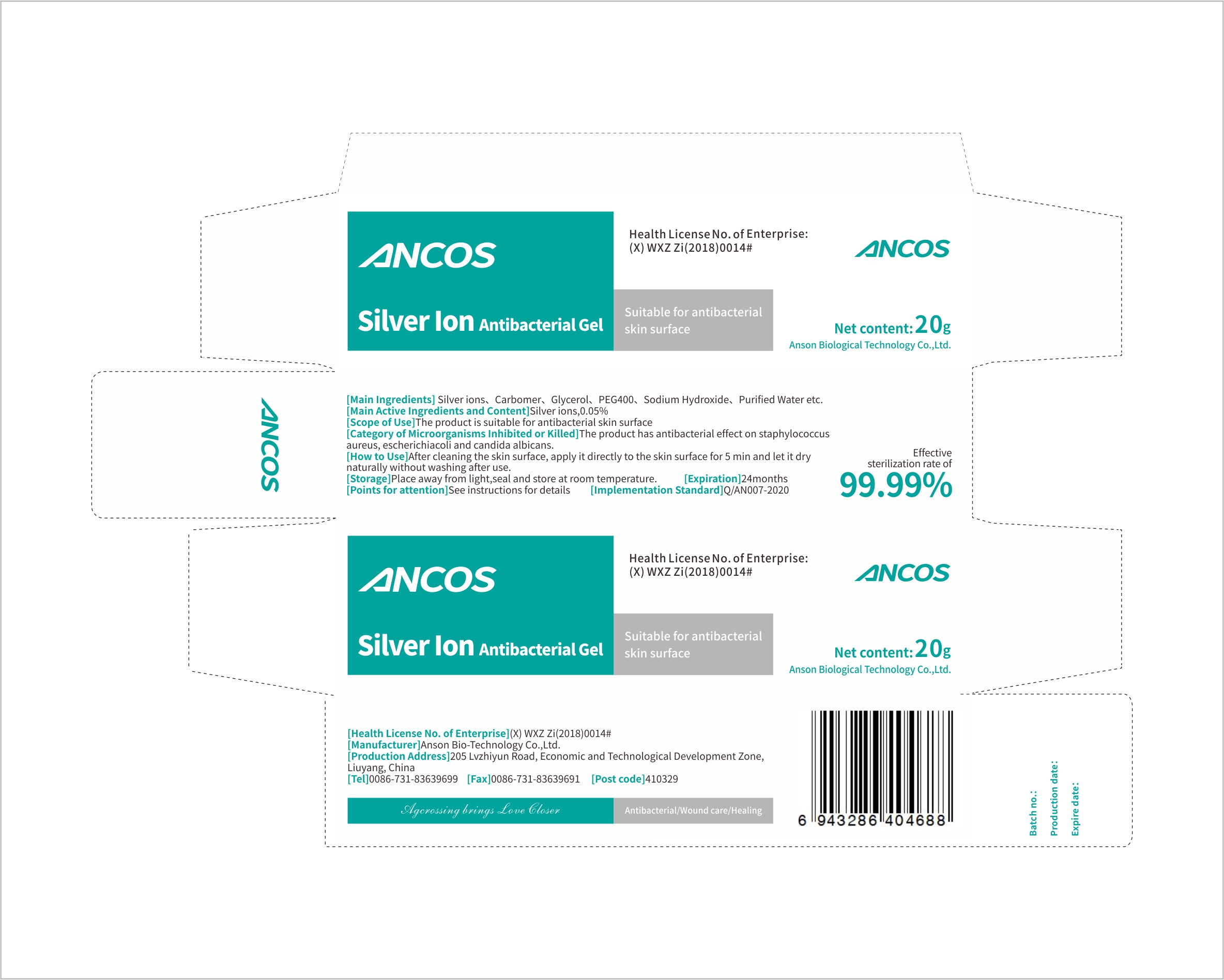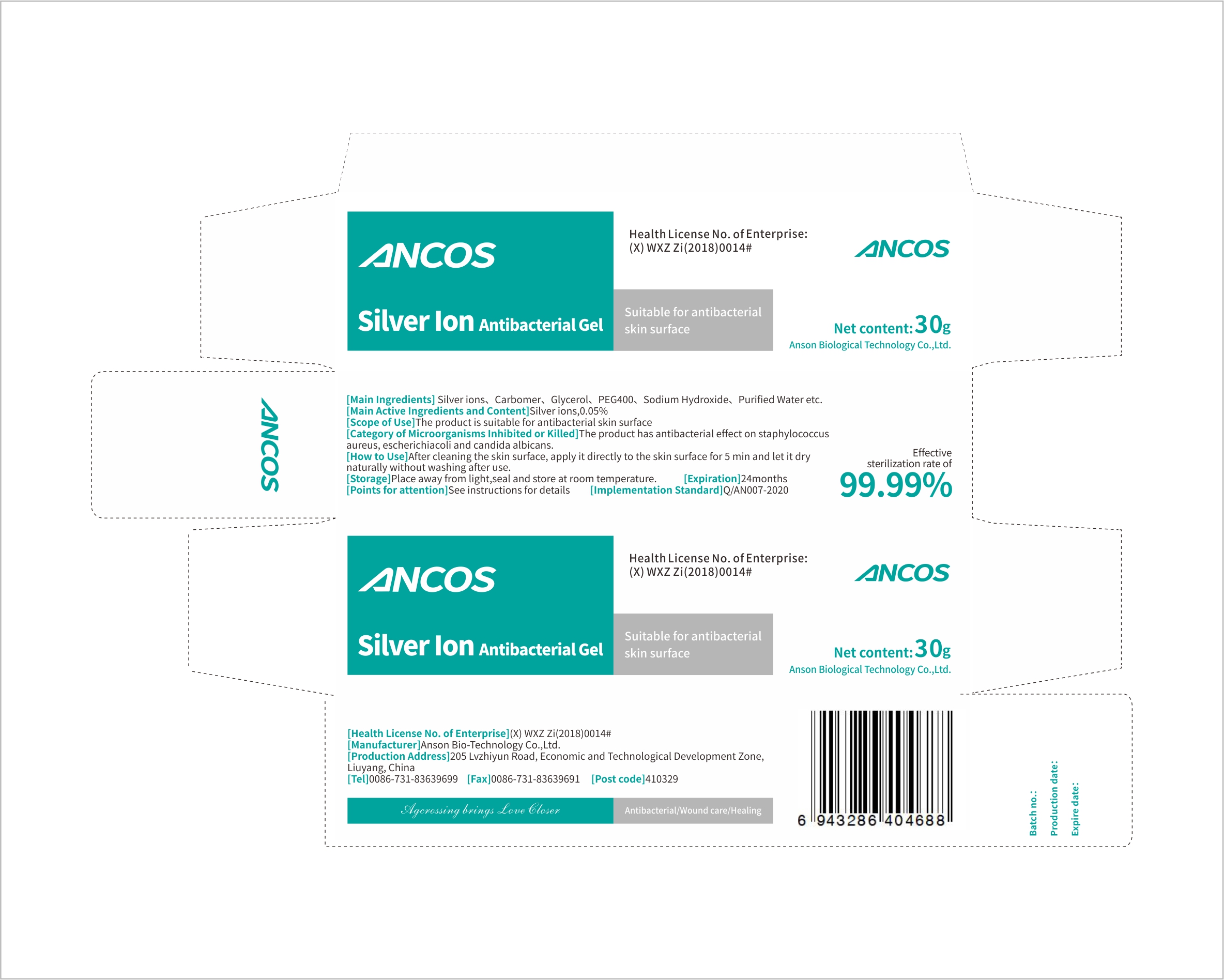 DRUG LABEL: Silver Ion Antibacterial Gel
NDC: 75139-007 | Form: GEL
Manufacturer: Anson Bio-Technology Co.,Ltd.
Category: otc | Type: HUMAN OTC DRUG LABEL
Date: 20210402

ACTIVE INGREDIENTS: GLYCERIN 5 g/100 g; SILVER CATION 0.05 g/100 g
INACTIVE INGREDIENTS: CARBOMER HOMOPOLYMER, UNSPECIFIED TYPE; WATER; SODIUM HYDROXIDE; POLYETHYLENE GLYCOL 400

75139-007
Silver Ion Antibacterial Gel

Main Active Ingredients and Content

Silver ions, 0.05%.

Glycerol, 5%.

Purpose

Antibacterial

Scope of Use

The product is suitable for antibacterial skin surface

Directions

After cleaning the skin surface, apply it directly to the skin surface for 5minandletitdry naturally without washing after use.

Warning

The product has antibacterial effect on staphylococcus aureus, escherichia coli and candida albicans.

Other Tips

Place away from light, seal and store at room temperature.

Precautions

See instructions for details

other ingredients

Carbomer, PEG 400, Sodium Hydroxide, Purified Water etc.

WHEN USING

See instructions for details

STOP USE

See instructions for details

KEEP OUT OF REACH OF CHILDREN

See instructions for details

Package Label - Principal Display Panel

75139-007-01 3G

75139-007-02 5G

75139-007-03 10G

75139-007-04 20

75139-007-05 30G